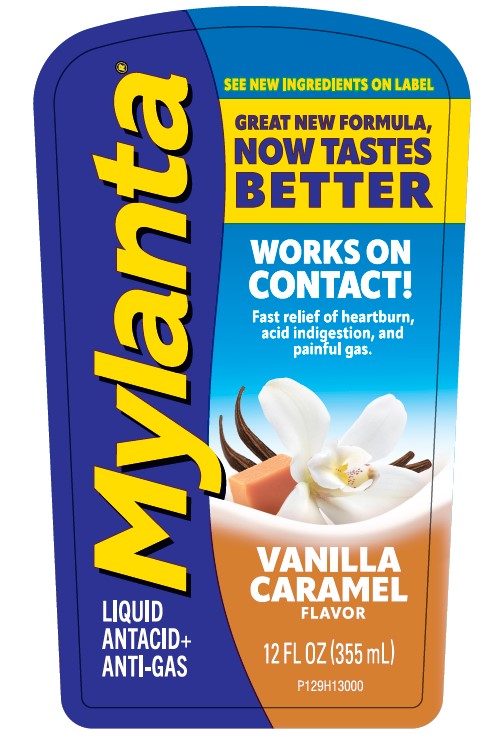 DRUG LABEL: Mylanta Vanilla Caramel
NDC: 62372-541 | Form: LIQUID
Manufacturer: Infirst Healthcare Inc.
Category: otc | Type: HUMAN OTC DRUG LABEL
Date: 20240205

ACTIVE INGREDIENTS: CALCIUM CARBONATE 800 mg/10 mL; DIMETHICONE 80 mg/10 mL; MAGNESIUM HYDROXIDE 270 mg/10 mL
INACTIVE INGREDIENTS: BENZYL ALCOHOL; XANTHAN GUM; GLYCERIN; GLYCERYL MONOSTEARATE; MICROCRYSTALLINE CELLULOSE; METHYLCELLULOSE, UNSPECIFIED; PEG-8 STEARATE; SODIUM BENZOATE; SORBIC ACID; SUCRALOSE; POLYSORBATE 65; EDETATE DISODIUM; WATER; BENZOIC ACID

Mylanta Vanilla Caramel

Active ingredients

Calcium carbonate 800 mg

Magnesium hydroxide 270 mg

Simethicone 80 mg

Purposes

Antacid

Antacid

Anti-gas

Uses

relieves:

• heartburn • acid indigestion • sour stomach

• upset stomach due to these symptoms

• pressure and bloating commonly referred to as gas

• overindulgence in food and drink

Warnings

Ask a doctor before use if you have

• kidney disease • a magnesium restricted diet

Ask a doctor or pharmacist before use if you are

presently taking a prescription drug. Antacids may interact with certain prescription drugs.

Keep out of reach of children.

In case of overdose, get medical help or contact a poison control center right away at 1-800-222-1222.

Directions

• shake well before use • measure with dosing cup provided

• adults and children 12 years and over:

10 mL-20 mL (1-2 doses) as needed, between meals, at bedtime or as directed by a doctor

• do not take more than 60 mL (6 doses) in any 24-hour period

• do not use the maximum dosage for more than 2 weeks

• children under 12 years: ask a doctor

• mL=milliliter

Other information

each 10 mL dose contains:

calcium 335 mg; magnesium 120 mg; sodium 8 mg

• store between 20-25°C (68-77°F), do not freeze

Inactive ingredients

benzoic acid, benzyl alcohol, edetate disodium, flavor, glycerin, glyceryl monostearate, methylcellulose, microcrystalline cellulose, peg-8 stearate, polysorbate 65, purified water, sodium benzoate, sorbic acid, sucralose, xanthan gum

Questions or comments?

call 1-844-695-6624 toll free (English and Spanish)

TAMPER EVIDENT: DO NOT USE IF PRINTED SEAL UNDER CAP IS BROKEN OR MISSING.

infirst^+

HEALTHCARE®

Manufactured for:

Infirst Healthcare Inc.

Westport, CT 06880

©2023 Infirst Healthcare Inc.

Mylanta.com

Lot:

Exp:

PACKAGE LABEL

Mylanta®

LIQUID ANTACID+ANTI-GAS

WORKS ON CONTACT!

Fast relief of heartburn, acid indigestion, and painful gas.

VANILLA CARAMEL FLAVOR

12 FL OZ (355 mL)